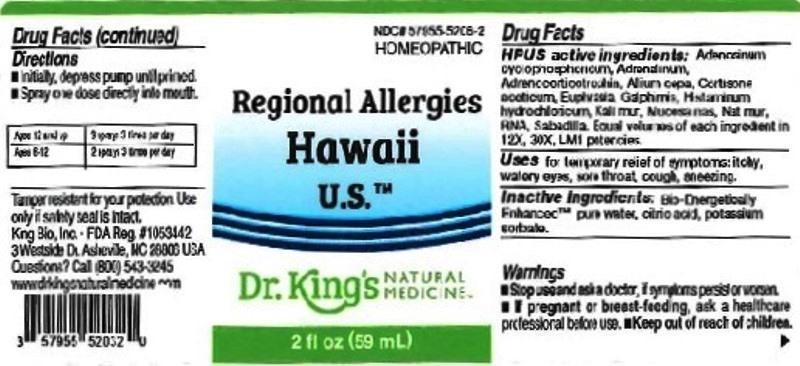 DRUG LABEL: Regional Allergies Hawaii U.S.
NDC: 57955-5206 | Form: LIQUID
Manufacturer: King Bio Inc.
Category: homeopathic | Type: HUMAN OTC DRUG LABEL
Date: 20160411

ACTIVE INGREDIENTS: ADENOSINE CYCLIC PHOSPHATE 12 [hp_X]/59 mL; EPINEPHRINE 12 [hp_X]/59 mL; CORTICOTROPIN 12 [hp_X]/59 mL; ONION 12 [hp_X]/59 mL; CORTISONE ACETATE 12 [hp_X]/59 mL; EUPHRASIA STRICTA 12 [hp_X]/59 mL; GALPHIMIA GLAUCA FLOWERING TOP 12 [hp_X]/59 mL; HISTAMINE DIHYDROCHLORIDE 12 [hp_X]/59 mL; POTASSIUM CHLORIDE 12 [hp_X]/59 mL; SUS SCROFA NASAL MUCOSA 12 [hp_X]/59 mL; SODIUM CHLORIDE 12 [hp_X]/59 mL; SACCHAROMYCES CEREVISIAE RNA 12 [hp_X]/59 mL; SCHOENOCAULON OFFICINALE SEED 12 [hp_X]/59 mL
INACTIVE INGREDIENTS: WATER; ANHYDROUS CITRIC ACID; POTASSIUM SORBATE

Regional Allergies Hawaii U.S.™

ACTIVE INGREDIENT

Drug Facts__________________________________________________________________________________________________________

HPUS active ingredients: Adenosinum cyclophosphoricum, Adrenalinum, Adrenocorticotrophin, Allium cepa, Cortisone aceticum, Euphrasia officinalis, Galphimia glauca, Histaminum hydrochloricum, Kali muriaticum, Mucosa nasalis suis, Natrum muriaticum, RNA, Sabadilla. Equal volumes of each ingredient in 12X, 30X, LM1 potencies.

INDICATIONS AND USAGE

Uses for temporary relief of symptoms: itchy, watery eyes, sore throat, cough, sneezing.

Inactive Ingredients:

Bio-Energetically Enhanced™ pure water, citric acid and potassium sorbate.

Warnings

- Stop use and ask your doctor if symptoms persist or worsen.
- If pregnant or breast-feeding, ask a healthcare professional before use.

- Keep out of reach of children.

Directions

- Initially, depress pump until primed.
- Spray one dose directly into mouth.
- Ages 12 and up: 3 sprays 3 times per day.
- Ages 6-12: 2 sprays 3 times per day.

OTHER SAFETY INFORMATION

Tamper resistant for your protection. Use only if seal is intact.

PURPOSE

Uses for temporary relief of symptoms:

- itchy
- watery eyes
- sore throat
- cough
- sneezing